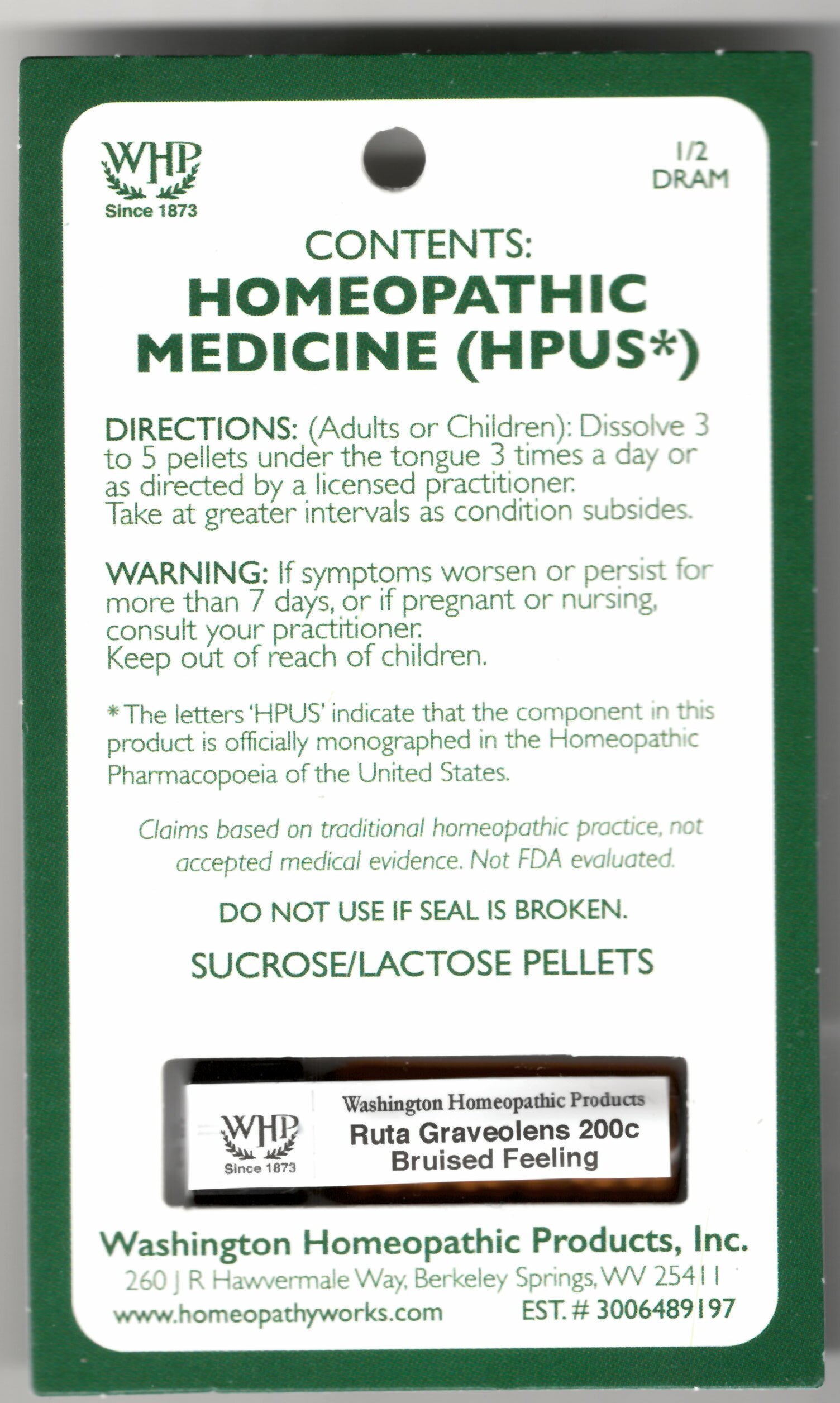 DRUG LABEL: Ruta Graveolens Kit Refill
NDC: 68428-068 | Form: PELLET
Manufacturer: Washington Homeopathic Products
Category: homeopathic | Type: HUMAN OTC DRUG LABEL
Date: 20240305

ACTIVE INGREDIENTS: RUTA GRAVEOLENS FLOWERING TOP 200 [hp_C]/1 1
INACTIVE INGREDIENTS: SUCROSE; LACTOSE

DRUG FACTS

USES

To relieve the symptoms of bruised feeling.

KEEP OUT OF REACH OF CHILDREN

Keep this and all medicines out of reach of children.

INDICATIONS

RUTA GRAVEOLENS Bruised feeling

STOP USE AND ASK DOCTOR

If symptoms persist/worsen or if pregnant/nursing, stop use and consult your practitioner.

DIRECTIONS

Adults: Dissolve 3 to 5 under the tongue three times a day or as directed by Lic. Practitioner. Take at greater intervals as condition subsides.

Children: Dissolve 3 to 5 under the tongue three times a day or as directed by Lic. Practitioner. Take at greater intervals as condition subsides.

INACTIVE INGREDIENTS

Sucrose/Lactose